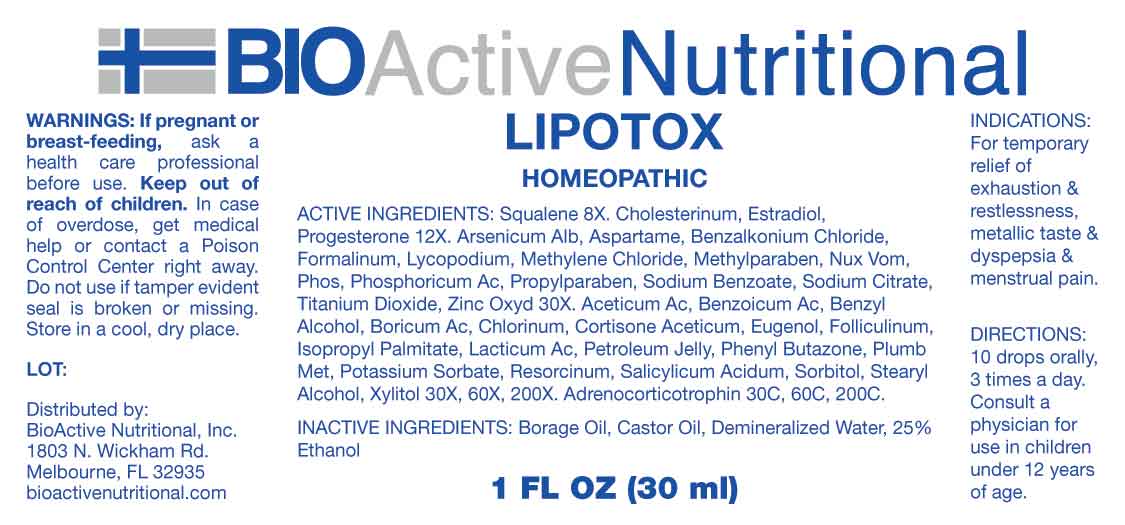 DRUG LABEL: Lipotox
NDC: 43857-0636 | Form: LIQUID
Manufacturer: BioActive Nutritional, Inc.
Category: homeopathic | Type: HUMAN OTC DRUG LABEL
Date: 20230905

ACTIVE INGREDIENTS: SQUALENE 8 [hp_X]/1 mL; CHOLESTEROL 12 [hp_X]/1 mL; ESTRADIOL 12 [hp_X]/1 mL; PROGESTERONE 12 [hp_X]/1 mL; ASPARTAME 30 [hp_X]/1 mL; BENZALKONIUM CHLORIDE 30 [hp_X]/1 mL; FORMALDEHYDE SOLUTION 30 [hp_X]/1 mL; METHYLENE CHLORIDE 30 [hp_X]/1 mL; METHYLPARABEN 30 [hp_X]/1 mL; PROPYLPARABEN 30 [hp_X]/1 mL; SODIUM BENZOATE 30 [hp_X]/1 mL; ANHYDROUS TRISODIUM CITRATE 30 [hp_X]/1 mL; TITANIUM DIOXIDE 30 [hp_X]/1 mL; ZINC OXIDE 30 [hp_X]/1 mL; ARSENIC TRIOXIDE 30 [hp_X]/1 mL; LYCOPODIUM CLAVATUM SPORE 30 [hp_X]/1 mL; STRYCHNOS NUX-VOMICA SEED 30 [hp_X]/1 mL; PHOSPHORIC ACID 30 [hp_X]/1 mL; PHOSPHORUS 30 [hp_X]/1 mL; ACETIC ACID 30 [hp_X]/1 mL; BENZOIC ACID 30 [hp_X]/1 mL; BENZYL ALCOHOL 30 [hp_X]/1 mL; BORIC ACID 30 [hp_X]/1 mL; CHLORINE 30 [hp_X]/1 mL; CORTISONE ACETATE 30 [hp_X]/1 mL; EUGENOL 30 [hp_X]/1 mL; ESTRONE 30 [hp_X]/1 mL; ISOPROPYL PALMITATE 30 [hp_X]/1 mL; LACTIC ACID, DL- 30 [hp_X]/1 mL; PETROLATUM 30 [hp_X]/1 mL; PHENYLBUTAZONE 30 [hp_X]/1 mL; LEAD 30 [hp_X]/1 mL; POTASSIUM SORBATE 30 [hp_X]/1 mL; RESORCINOL 30 [hp_X]/1 mL; SALICYLIC ACID 30 [hp_X]/1 mL; SORBITOL 30 [hp_X]/1 mL; STEARYL ALCOHOL 30 [hp_X]/1 mL; XYLITOL 30 [hp_X]/1 mL; CORTICOTROPIN 30 [hp_C]/1 mL
INACTIVE INGREDIENTS: BORAGE OIL; CASTOR OIL; WATER; ALCOHOL

DRUG FACTS:

ACTIVE INGREDIENTS:

Squalene 8X, Cholesterinum 12X, Estradiol 12X, Progesterone 12X, Aspartame 30X, Benzalkonium Chloride 30X, Formalinum 30X, Methylene Chloride 30X, Methylparaben 30X, Propylparaben 30X, Sodium Benzoate 30X, Sodium Citrate 30X, Titanium Dioxide 30X, Zincum Oxydatum 30X, Arsenicum Album 30X, Lycopodium Clavatum 30X, Nux Vomica 30X, Phosphoricum Acidum 30X, Phosphorus 30X, Aceticum Acidum 30X, 60X, 200X, Benzoicum Acidum 30X, 60X, 200X, Benzyl Alcohol 30X, 60X, 200X, Boricum Acidum 30X, 60X, 200X, Chlorinum 30X, 60X, 200X, Cortisone Aceticum 30X, 60X, 200X, Eugenol 30X, 60X, 200X, Folliculinum 30X, 60X, 200X, Isopropyl Palmitate 30X, 60X, 200X, Lacticum Acidum 30X, 60X, 200X, Petroleum Jelly 30X, 60X, 200X, Phenyl Butazone 30X, 60X, 200X, Plumbum Metallicum 30X, 60X, 200X, Potassium Sorbate 30X, 60X, 200X, Resorcinum 30X, 60X, 200X, Salicylicum Acidum 30X, 60X, 200X, Sorbitol 30X, 60X, 200X, Stearyl Alcohol 30X, 60X, 200X, Xylitol 30X, 60X, 200X, Adrenocorticotrophin 30C, 60C, 200C.

PURPOSE:

For temporary relief of exhaustion & restlessness, metallic taste & dyspepsia & menstrual pain.

WARNINGS:

If pregnant or breast-feeding, ask a health care professional before use.
Keep out of reach of children. In case of overdose, get medical help or contact a Poison Control Center right away.
Do not use if tamper evident seal is broken or missing.
Store in cool, dry place.

KEEP OUT OF REACH OF CHILDREN:

In case of overdose, get medical help or contact a Poison Control Center right away.

DIRECTIONS:

10 drops orally, 3 times a day. Consult a physician for use in children under 12 years of age.

INDICATIONS:

For temporary relief of exhaustion & restlessness, metallic taste & dyspepsia & menstrual pain.

INACTIVE INGREDIENTS:

Borage Oil, Castor Oil, Demineralized Water, 25% Ethanol.

QUESTIONS:

Distributed by:

BioActive Nutritional, Inc.

1803 N. Wickham Rd.

Melbourne, FL 32935

bioactivenutritional.com

PACKAGE LABEL DISPLAY:

BIOActiveNutritional

LIPOTOX

HOMEOPATHIC

1 FL OZ (30 ml)